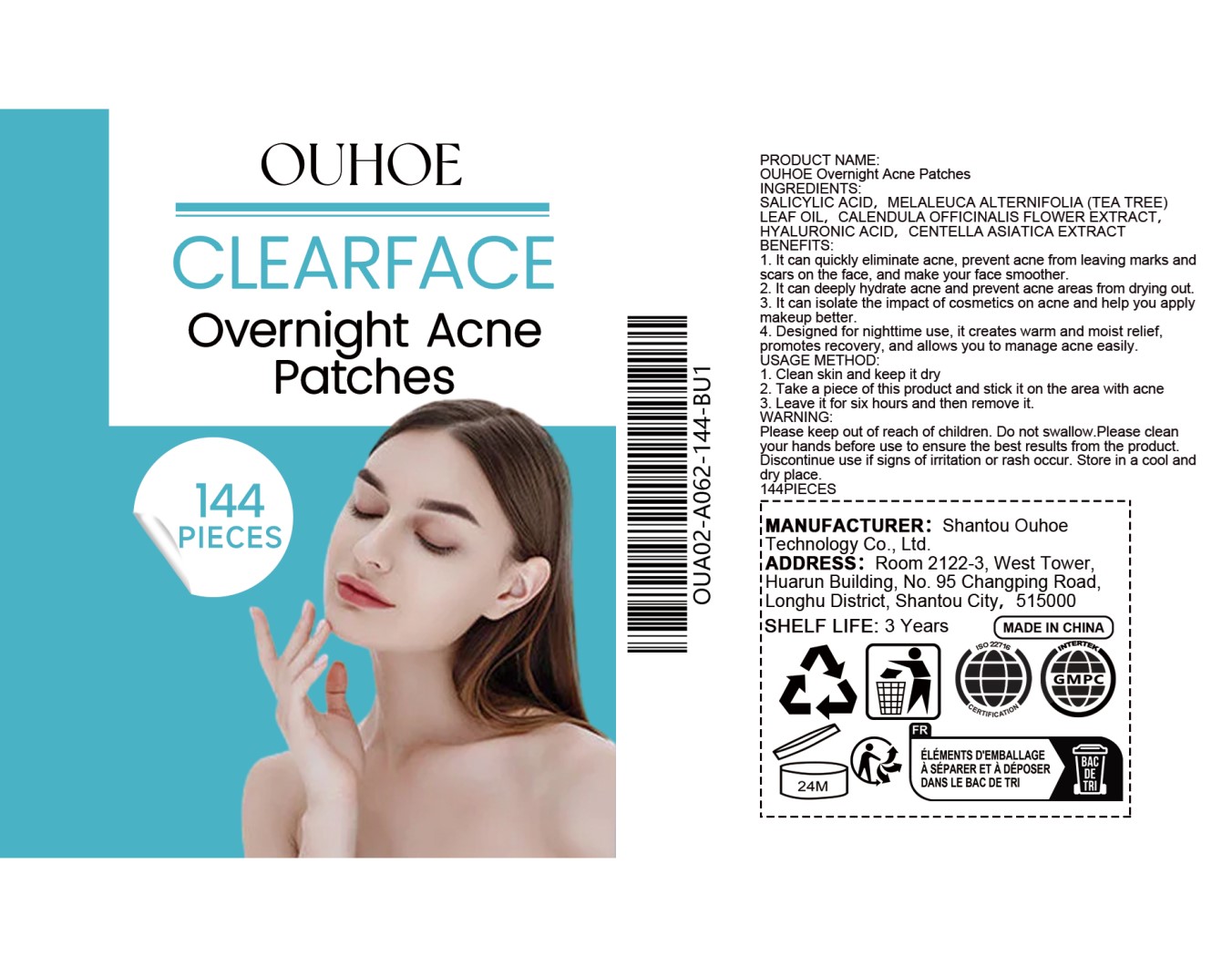 DRUG LABEL: OUHOE CLEARFACE Overnight Acne
NDC: 85163-001 | Form: PATCH
Manufacturer: Shantou Ouhoe Technology Co., Ltd.
Category: otc | Type: HUMAN OTC DRUG LABEL
Date: 20251127

ACTIVE INGREDIENTS: SALICYLIC ACID 0.02 g/100 g
INACTIVE INGREDIENTS: TEA TREE OIL; CALENDULA OFFICINALIS FLOWER; HYALURONIC ACID; CENTELLA ASIATICA TRITERPENOIDS

INGREDIENTS

SALICYLIC ACID, MELALEUCA ALTERNIFOLIA (TEA TREE)
LEAF OIL, CALENDULA OFFICINALIS FLOWER EXTRACT,
HYALURONIC ACID， CENTELLA ASIATICA EXTRACT

BENEFITS:

1. lt can quickly eliminate acne, prevent acne from leaving marks andscars on the face, and make your face smoother.

2. lt can deeply hydrate acne and prevent acne areas from drying out.

3. lt can isolate the impact of cosmetics on acne and help you applymakeup better.

4.Designed for nighttime use, it creates warm and moist relief.promotes recovery,and allows you to manage acne easily.

INDICATIONS AND USAGE

none

Warning

Please keep out of reach of children. Do not swallow.Please cleanyour hands before use to ensure the best results from the product.Discontinue use if signs of irritation or rash occur. Store in a cool anddry place.

DO NOT USE

none

warning

Please clean your hands before use to ensure the best results from the product.

Warning

Discontinue use if signs of irritation or rash occur.

warning

Please keep out of reach of children

Usage Method

1. Clean skin and keep it dry

2. Take a piece of this product and stick it on the area with acne

3. Leave it for six hours and then remove it.

warning

Store in a cool anddry place.

INACTIVE INGREDIENT

NONE